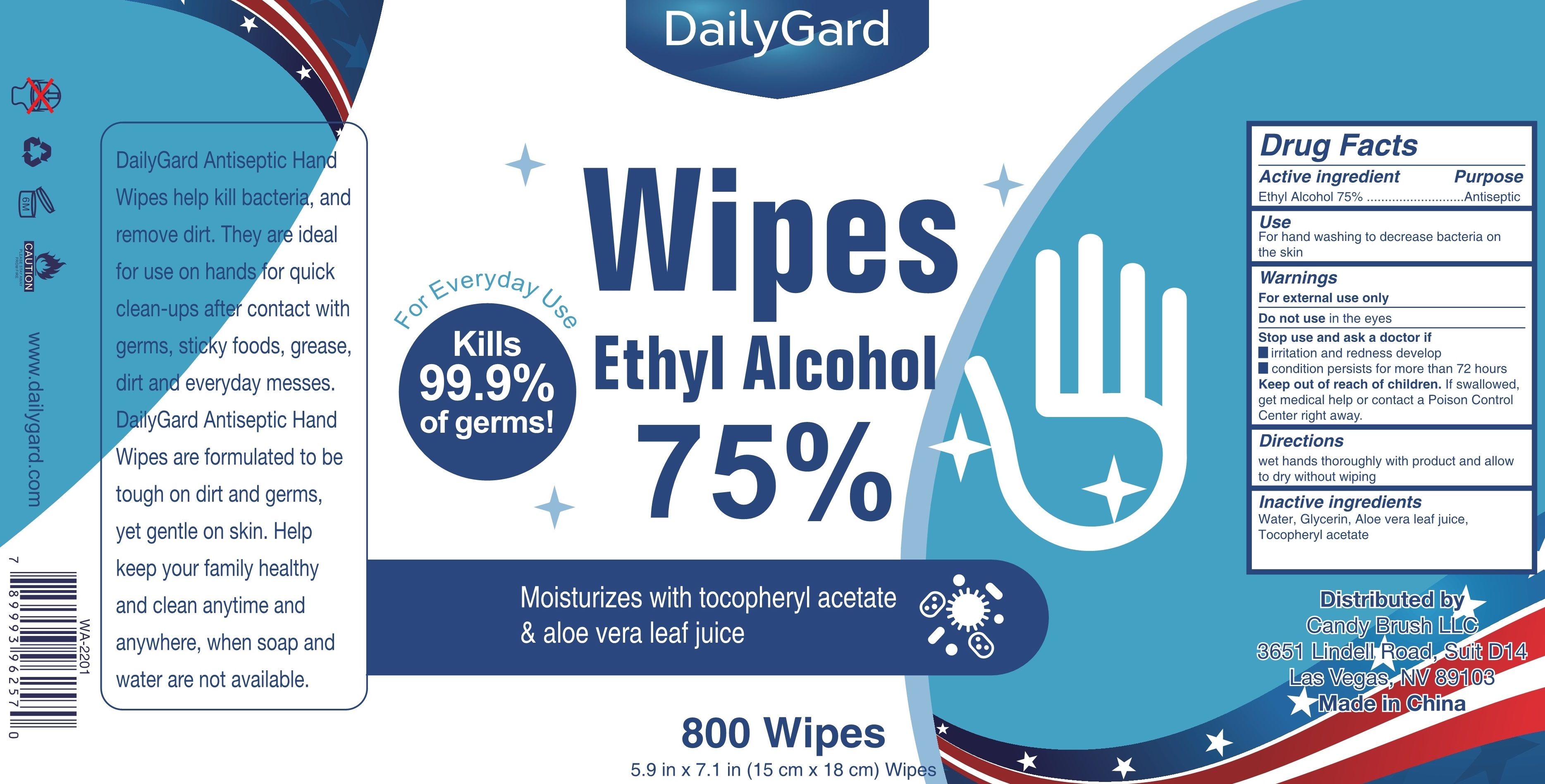 DRUG LABEL: Ethyl Alcohol Wipes
NDC: 80110-017 | Form: CLOTH
Manufacturer: Anhui Germaphob Daily Commodity Co., Ltd.
Category: otc | Type: HUMAN OTC DRUG LABEL
Date: 20220105

ACTIVE INGREDIENTS: ALCOHOL 75 mL/100 1
INACTIVE INGREDIENTS: ALOE VERA LEAF; GLYCERIN; ALPHA-TOCOPHEROL ACETATE; WATER

80110-017
80110-016 replaced by 80110-017
Ethyl Alcohol Wipes

Active Ingredient(s)

Ethyl Alcohol75%

Purpose

Antiseptic

Use

For hand washing to decrease bacteria on the skin

Warnings

For external use only

Do not use in the eyes

Stop use and ask a doctor if
irritation and redness develop
condition persists for more than 72 hours

Keep out of reach of children. If swallowed, get medical help or contact a Poison Control Center right away.

Do not use in the eyes

When using this product Stop use and ask a doctor if
irritation and redness develop
condition persists for more than 72 hours

Keep out of reach of children. If swallowed, get medical help or contact a Poison Control Center right away.

Stop use and ask a doctor if
irritation and redness develop
condition persists for more than 72 hours

Keep out of reach of children. If swallowed, get medical help or contact a Poison Control Center right away.

Directions

wet hands thoroughly with product and allow to dry without wiping

Other information

/

Inactive ingredients

Water, Glycerin, Aloe vera leaf juice, Tocopheryl acetate